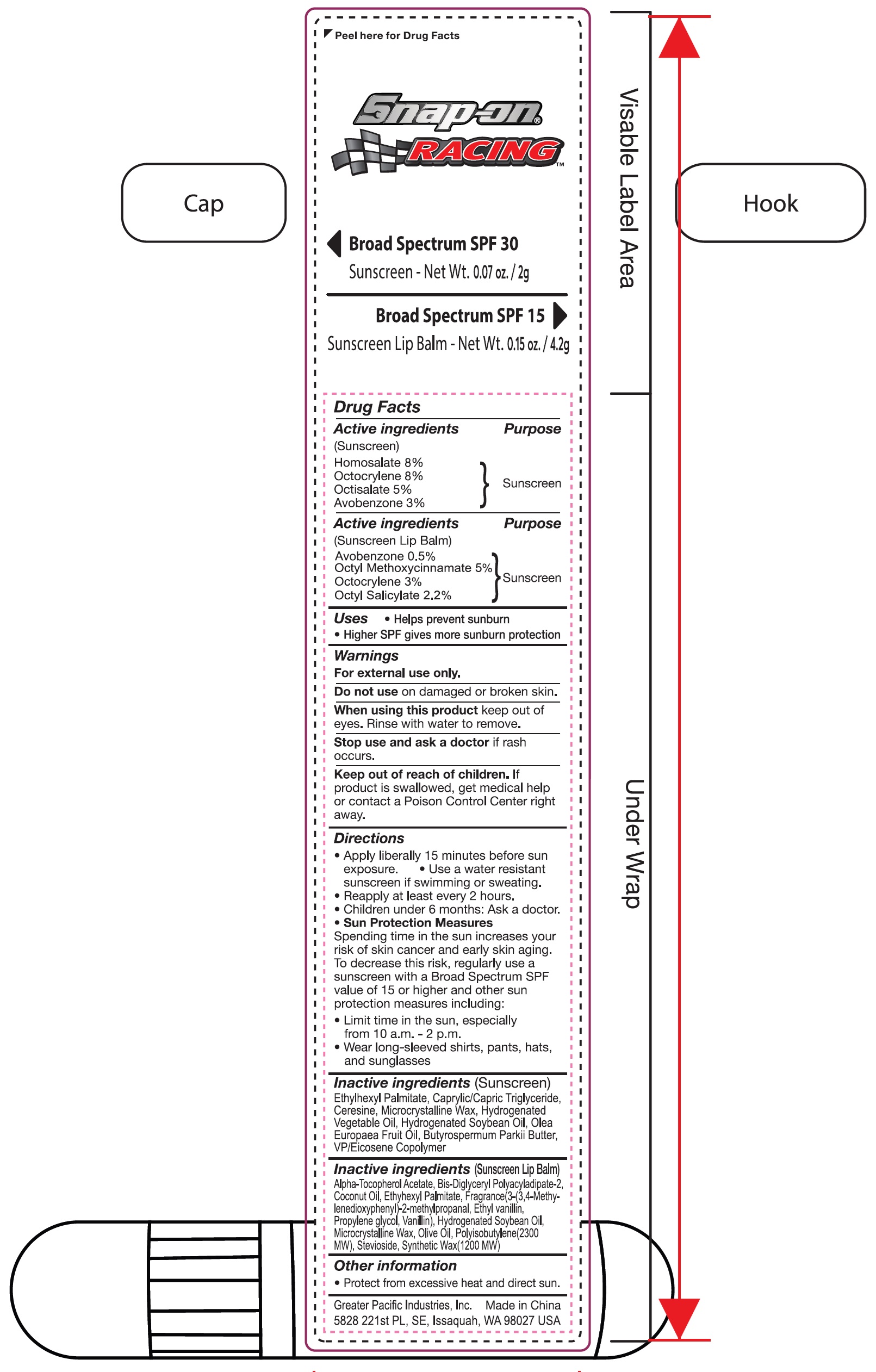 DRUG LABEL: Snap On Racing Sunscreen Kit
NDC: 85204-000 | Form: KIT | Route: TOPICAL
Manufacturer: Greater Pacific Industries, Inc.
Category: otc | Type: HUMAN OTC DRUG LABEL
Date: 20250116

ACTIVE INGREDIENTS: AVOBENZONE 5 mg/1 g; OCTINOXATE 50 mg/1 g; OCTOCRYLENE 30 mg/1 g; OCTISALATE 22 mg/1 g; HOMOSALATE 80 mg/1 g; OCTOCRYLENE 80 mg/1 g; OCTISALATE 50 mg/1 g; AVOBENZONE 30 mg/1 g
INACTIVE INGREDIENTS: ALPHA-TOCOPHEROL ACETATE; BIS-DIGLYCERYL POLYACYLADIPATE-2; COCONUT OIL; ETHYLHEXYL PALMITATE; 3-(3,4-METHYLENEDIOXYPHENYL)-2-METHYLPROPANAL; ETHYL VANILLIN; PROPYLENE GLYCOL; VANILLIN; HYDROGENATED SOYBEAN OIL; MICROCRYSTALLINE WAX; OLIVE OIL; STEVIOSIDE; SYNTHETIC WAX (1200 MW); POLYISOBUTYLENE (2300 MW); ETHYLHEXYL PALMITATE; CAPRYLIC/CAPRIC TRIGLYCERIDE; SODIUM DICHLOROACETATE; MICROCRYSTALLINE WAX; HYDROGENATED SOYBEAN OIL; OLIVE OIL

Snap-On Racing Sunscreen Kit

Active ingredients(Sunscreen Lip Balm)

Avobenzone 0.5%

Octyl Methoxycinnamate 5%

Octocrylene 3%

Octyl Salicylate 2.2%

Purpose

Sunscreen

Uses

- Helps prevent sunburn
- Higher SPF gives more sunburn protection

Warnings

For external use only.

Do not use

on damaged or broken skin.

When using this product

Keep out of eyes. Rinse with water to remove.

Stop use and ask a doctor

if rash occurs.

Keep out of reach of children.

If product is swallowed, get medical help or contact a Poison Control Center right away.

Directions

- Apply liberally 15 minutes before use exposure.
- Use a water resistant sunscreen if swimming or sweating.
- Reapply at least every 2 hours.
- Children under 6 months: Ask a doctor.
- Sun Protection MeasuresSpending time in the sun increases your risk of skin cancer and early skin aging. To decrease this risk, regularly use a sunscreen with a Broad Spectrum SPF value of 15 or higher and other sun protection measures including:
- Limit time in the sun, especially from 10 a.m. - 2 p.m.
- Wear long-sleeved shirts, pants, hats, and sunglasses

Inactive ingredients(Sunscreen Lip Balm)

Alpha-Tocopherol Acetate, Bis-Diglyceryl Polyacyladipate-2, Coconut Oil, Ethylhexyl Palmitate, Fragrance(3-(3,4-Methylenedioxyphenyl)-2 methylpropanal, Ethyl Vanillin, Propylene glycol, Vanillin), Hydrogenated Soybean Oil, Microcrystalline Wax, Olive Oil, Polysibutene(2300 MW), Stevioside, Synthetic Wax(1200 MW)

Other information

- Protect from excessive heat and direct sun.

Active ingredients(Sunscreen)

Homosalate 8%

Octocrylene 8%

Octisalate 5%

Avobenzone 3%

Purpose

Sunscreen

Uses

- Helps prevent sunburn
- Higher SPF gives more sunburn protection

Warnings

For external use only.

Do not use

on damaged or broken skin.

When using this product

keep out of eyes. Rinse with water to remove.

Stop use and ask a doctor

if rash occurs.

Keep out of reach of children.

If product is swallowed, get medical help or contact a Poison Control Center right away.

Directions

- Apply liberally 15 minutes before sun exposure.
- Use a water resistant sunscreen if swimming or sweating.
- Reapply at least every 2 hours.
- Children under 6 months: Ask a doctor.
- Sun Protection MeasuresSpending time in the sun increases your risk of skin cancer and early skin aging. To decrease this risk, regularly use a sunscreen with a Broad Spectrum SPF value of 15 or higher and other sun protection measures including:
- Limit time in the sun, especially from 10 a.m. - 2 p.m.
- Wear long-sleeved shirts, pants, hats, and sunglasses

Inactive ingredients(Sunscreen)

Ethylhexyl Palmitate, Caprylic/Capric Triglyceride, Ceresine, Microcrystalline Wax, Hydrogenated Vegetable Oil, Hydrogenated Soybean Oil, Olea Europaea Fruit Oil, Butyrospermum Parkii Butter, VP/Eicosene Copolymer

Other information

- Protect from excessive heat and direct sun.